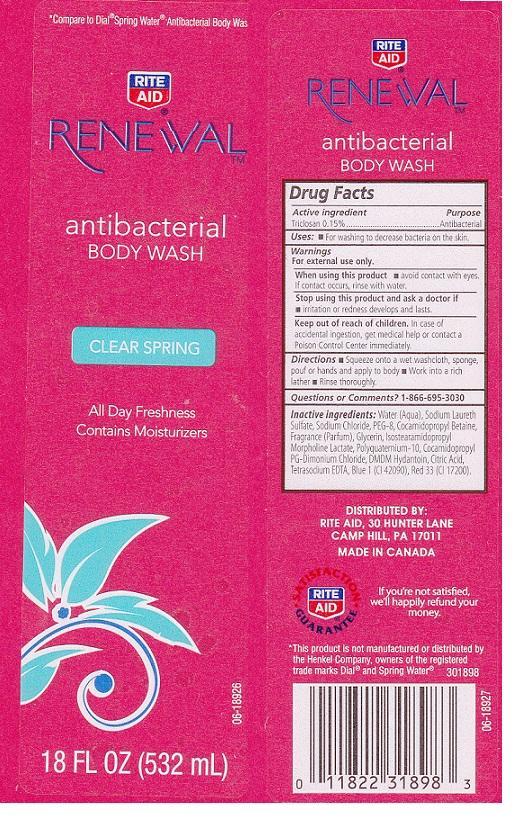 DRUG LABEL: RITE AID RENEWAL
NDC: 11822-8071 | Form: LIQUID
Manufacturer: RITE AID CORPORATION
Category: otc | Type: HUMAN OTC DRUG LABEL
Date: 20130703

ACTIVE INGREDIENTS: TRICLOSAN 1.5 mg/1 mL
INACTIVE INGREDIENTS: WATER; SODIUM LAURETH SULFATE; SODIUM CHLORIDE; POLYETHYLENE GLYCOL 400; COCAMIDOPROPYL BETAINE; GLYCERIN; ISOSTEARAMIDOPROPYL MORPHOLINE LACTATE; POLYQUATERNIUM-10 (400 CPS AT 2%); COCAMIDOPROPYL PG-DIMONIUM CHLORIDE; DMDM HYDANTOIN; CITRIC ACID MONOHYDRATE; EDETATE SODIUM; FD&C BLUE NO. 1; D&C RED NO. 33

DRUG FACTS

ACTIVE INGREDIENT

TRICLOSAN 0.15%

PURPOSE

ANTIBACTERIAL

USES

FOR WASHING TO DECREASE BACTERIA ON THE SKIN.

WARNINGS

FOR EXTERNAL USE ONLY.

WHEN USING THIS PRODUCT

AVOID CONTACT WITH EYES. IF CONTACT OCCURS, RINSE WITH WATER.

STOP USING THIS PRODUCT AND ASK A DOCTOR IF

IRRITATION OR REDNESS DEVELOPS AND LASTS.

KEEP OUT OF REACH OF CHILDREN

IN CASE OF ACCIDENTAL INGESTION, GET MEDICAL HELP OR CONTACT A POISON CONTROL CENTER IMMEDIATELY.

DIRECTIONS

SQUEEZE ONTO A WET WASHCLOTH, SPONGE, POUF OR HANDS AND APPLY TO BODY. WORK INTO A RICH LATHER. RINSE THOROUGHLY.

QUESTIONS OR COMMENTS?

1-866-695-3030

INACTIVE INGREDIENTS:

WATER (AQUA), SODIUM LAURETH SULFATE, SODIUM CHLORIDE, PEG-8, COCAMIDOPROPYL BETAINE, FRAGRANCE (PARFUM), GLYCERIN, ISOSTEARAMIDOPROPYL MORPHOLINE LACTATE, POLYQUATERNIUM-10, COCAMIDOPROPYL PG-DIMONIUM CHLORIDE, DMDM HYDANTOIN, CITRIC ACID, TETRASODIUM EDTA, BLUE 1 (CI 42090), RED 33 (CI 17200).